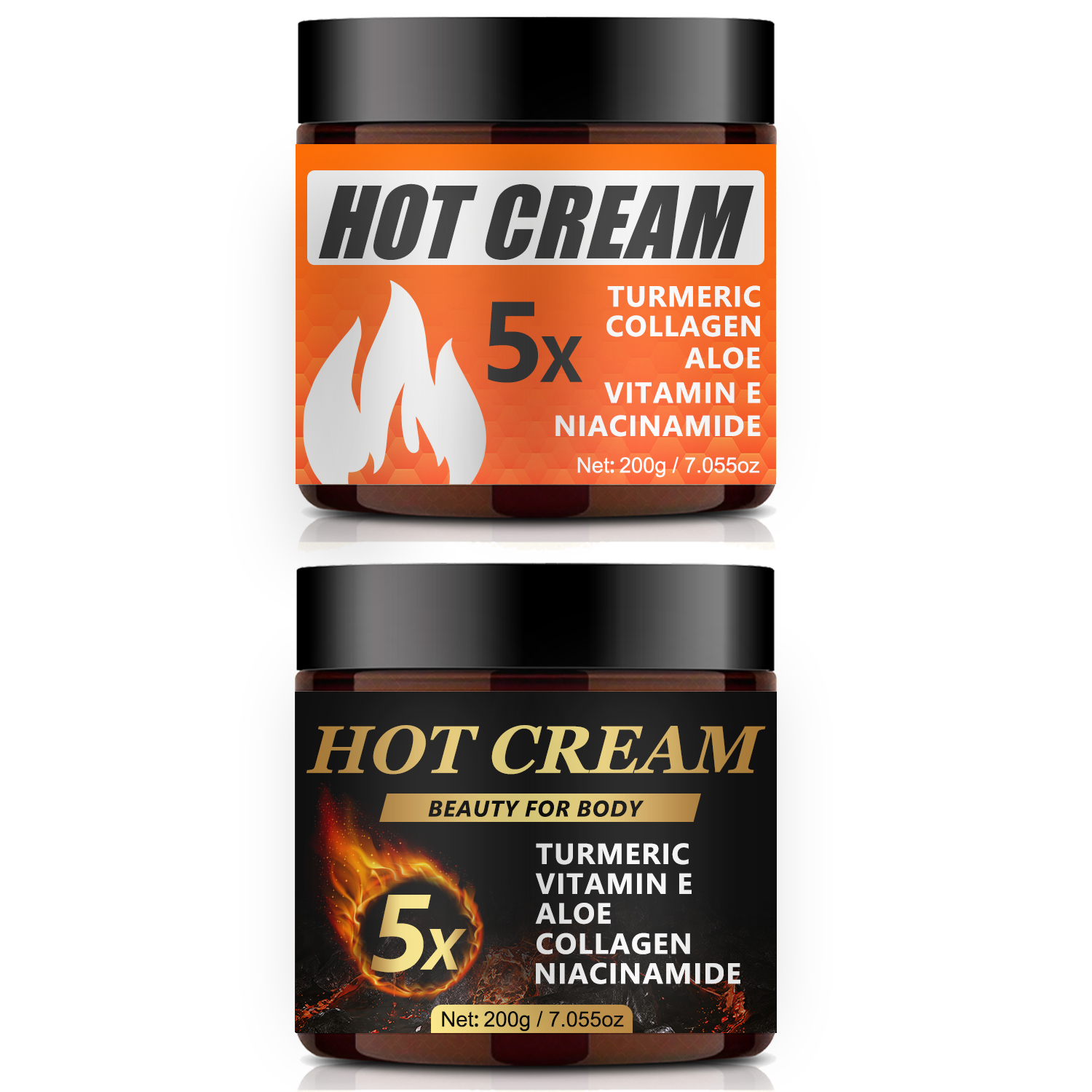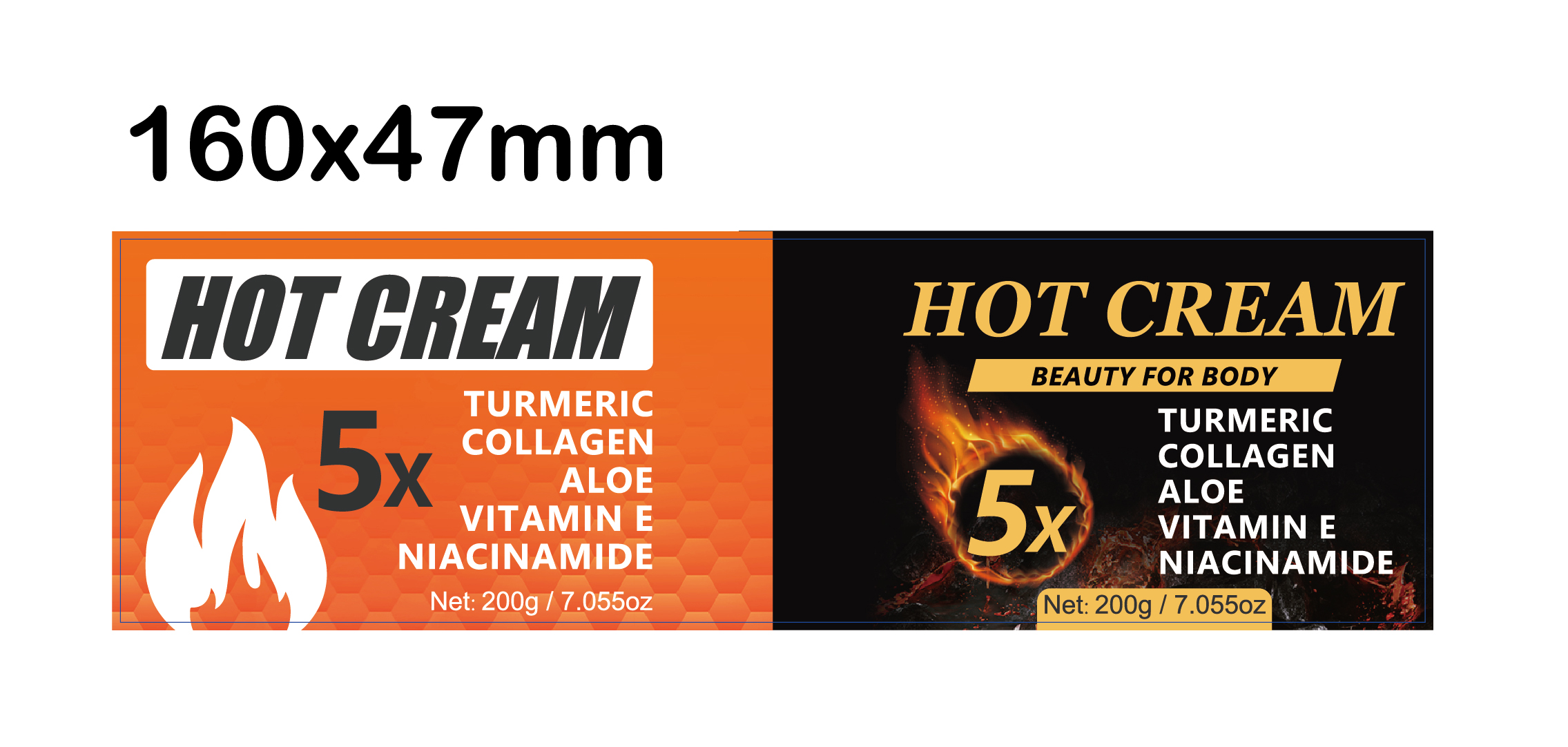 DRUG LABEL: Hot Cream
NDC: 84025-194 | Form: CREAM
Manufacturer: Guangzhou Yanxi Biotechnology Co.. Ltd
Category: otc | Type: HUMAN OTC DRUG LABEL
Date: 20240925

ACTIVE INGREDIENTS: ISOPROPYL PALMITATE 3 mg/200 g; GLYCERIN 5 mg/200 g
INACTIVE INGREDIENTS: WATER

DOSAGE AND ADMINISTRATION

Cream for moisturizing the skin

INDICATIONS AND USAGE

For daily skin care

INACTIVE INGREDIENT

AUQA

WARNINGS

keep out of children

keep out of children

PURPOSE

For moisturizing the skin